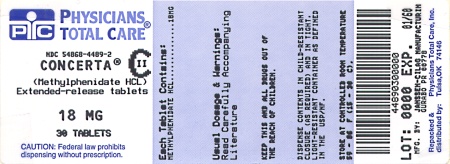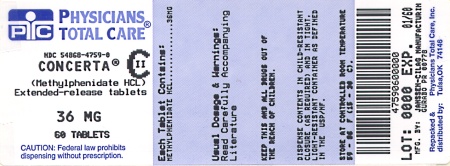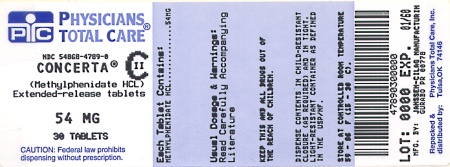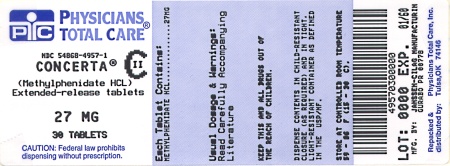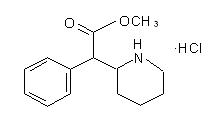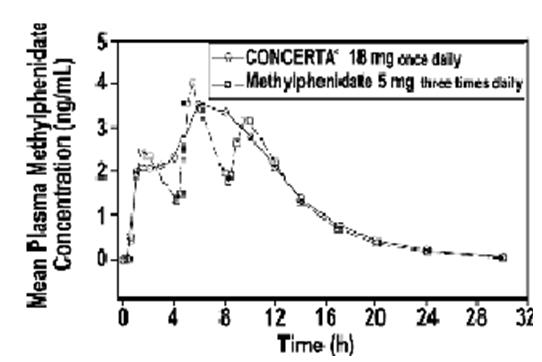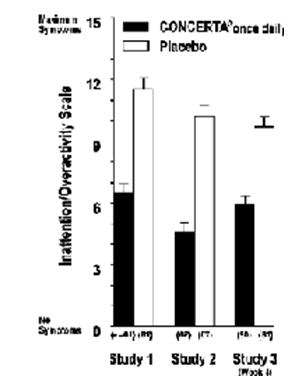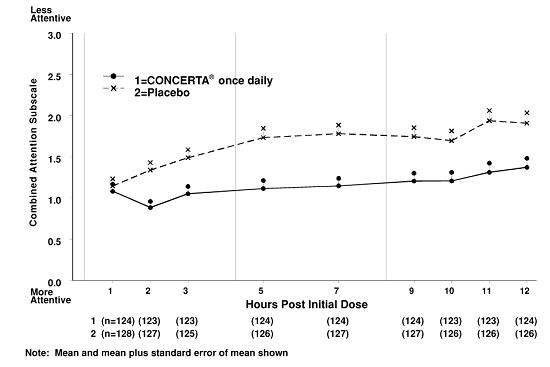 DRUG LABEL: Concerta
NDC: 54868-4489 | Form: TABLET, EXTENDED RELEASE
Manufacturer: Physicians Total Care, Inc.
Category: prescription | Type: HUMAN PRESCRIPTION DRUG LABEL
Date: 20101101
DEA Schedule: CII

ACTIVE INGREDIENTS: METHYLPHENIDATE HYDROCHLORIDE 18 mg/1 1
INACTIVE INGREDIENTS: BUTYLATED HYDROXYTOLUENE; CARNAUBA WAX; HYPROMELLOSES; LACTOSE; PHOSPHORIC ACID; POLYETHYLENE GLYCOL; POVIDONE; PROPYLENE GLYCOL; SODIUM CHLORIDE; STEARIC ACID; SUCCINIC ACID; FERROSOFERRIC OXIDE; TITANIUM DIOXIDE; TRIACETIN; CELLULOSE ACETATE

HIGHLIGHTS OF PRESCRIBING INFORMATION

These highlights do not include all the information needed to use CONCERTA® safely and effectively. See full prescribing information for CONCERTA®.
CONCERTA® (methylphenidate HCl) Extended-Release Tablets CII
Initial U.S. Approval: 2000

DRUG DEPENDENCE

WARNING: DRUG DEPENDENCE

See full prescribing information for complete boxed warning.

CONCERTA® should be given cautiously to patients with a history of drug dependence or alcoholism. Chronic abusive use can lead to marked tolerance and psychological dependence, with varying degrees of abnormal behavior.

1 INDICATIONS AND USAGE

CONCERTA® is a CNS stimulant indicated for the treatment of Attention Deficit Hyperactivity Disorder (ADHD) in children 6 years of age and older, adolescents, and adults up to the age of 65. (1)

2 DOSAGE AND ADMINISTRATION

- CONCERTA® should be taken once daily in the morning and swallowed whole with the aid of liquids. CONCERTA® should not be chewed or crushed. CONCERTA® may be taken with or without food. (2.1)
- For children and adolescents new to methylphenidate, the recommended starting dosage is 18 mg once daily. Dosage may be increased by 18 mg/day at weekly intervals and should not exceed 54 mg/day in children and 72 mg/day in adolescents. (2.2)
- For adult patients new to methylphenidate, the recommended starting dose is 18 or 36 mg/day. Dosage may be increased by 18 mg/day at weekly intervals and should not exceed 72 mg/day for adults. (2.2)
- For patients currently using methylphenidate, dosing is based on current dose regimen and clinical judgment. (2.3)

3 DOSAGE FORMS AND STRENGTHS

Tablets: 18, 27, 36, and 54 mg (3)

4 CONTRAINDICATIONS

Known hypersensitivity to the product (4.1)

Marked anxiety, tension, or agitation (4.2)

- Glaucoma (4.3)
- Tics or a family history or diagnosis of Tourette's syndrome (4.4)
- Do not use CONCERTA® in patients currently using or within 2 weeks of using an MAO inhibitor (4.5)

5 WARNINGS AND PRECAUTIONS

- Serious Cardiovascular Events: Sudden death has been reported in association with CNS stimulant treatment at usual doses in children and adolescents with structural cardiac abnormalities or other serious heart problems. Sudden death, stroke, and myocardial infarction have been reported in adults taking stimulant drugs at usual doses for ADHD. Stimulant products generally should not be used in patients with known structural cardiac abnormalities, cardiomyopathy, serious heart rhythm abnormalities, coronary artery disease, or other serious heart problems. (5.1)
- Increase in Blood Pressure: Monitor patients for changes in heart rate and blood pressure and use with caution in patients for whom an increase in blood pressure or heart rate would be problematic. (5.1)
- Psychiatric Adverse Events: Use of stimulants may cause treatment-emergent psychotic or manic symptoms in patients with no prior history, or exacerbation of symptoms in patients with preexisting psychiatric illness. Clinical evaluation for Bipolar Disorder is recommended prior to stimulant use. Monitor for aggressive behavior. (5.2)
- Seizures: Stimulants may lower the convulsive threshold. Discontinue in the presence of seizures. (5.3)
- Visual Disturbance: difficulties with accommodation and blurring of vision have been reported with stimulant treatment. (5.5)
- Long-Term Suppression of Growth: monitor height and weight at appropriate intervals in pediatric patients. (5.4)
- Gastrointestinal obstruction with preexisting GI narrowing. (5.6)
- Hematologic monitoring: Periodic CBC, differential, and platelet counts are advised during prolonged therapy. (5.7)

6 ADVERSE REACTIONS

The most common adverse reaction in double-blind clinical trials (>5%) in children and adolescents was abdominal pain upper. The most common adverse reactions in double-blind clinical trials (>5%) in adult patients were decreased appetite, headache, dry mouth, nausea, insomnia, anxiety, dizziness, weight decreased, irritability, and hyperhidrosis. (6.1 and 6.2)

The most common adverse reactions associated with discontinuation (≥1%) from either pediatric or adult clinical trials were anxiety, irritability, insomnia, and blood pressure increased. (6.3)

To report SUSPECTED ADVERSE REACTIONS, contact McNeil Pediatrics at 1-888-440-7903 or FDA at 1-800-FDA-1088 or www.fda.gov/medwatch.

7 DRUG INTERACTIONS

- Do not use CONCERTA® in patients currently using or within 2 weeks of using an MAO inhibitor (7.1)
- CONCERTA® may increase blood pressure; use cautiously with vasopressors (7.2)
- Inhibition of metabolism of coumarin anticoagulants, anticonvulsants, and some antidepressants (7.3)

8 USE IN SPECIFIC POPULATIONS

Caution should be exercised if administered to nursing mothers (8.3)

- Safety and efficacy has not been established in children less than six years old or elderly patients greater than 65 years of age (8.4 and 8.5)

FULL PRESCRIBING INFORMATION

DRUG DEPENDENCE

CONCERTA® should be given cautiously to patients with a history of drug dependence or alcoholism. Chronic abusive use can lead to marked tolerance and psychological dependence with varying degrees of abnormal behavior. Frank psychotic episodes can occur, especially with parenteral abuse. Careful supervision is required during withdrawal from abusive use since severe depression may occur. Withdrawal following chronic therapeutic use may unmask symptoms of the underlying disorder that may require follow-up.

1 INDICATIONS AND USAGE

CONCERTA® is indicated for the treatment of Attention Deficit Hyperactivity Disorder (ADHD) in children 6 years of age and older, adolescents, and adults up to the age of 65 [see Clinical Studies (14)].

A diagnosis of Attention Deficit Hyperactivity Disorder (ADHD; DSM-IV) implies the presence of hyperactive-impulsive or inattentive symptoms that caused impairment and were present before age 7 years. The symptoms must cause clinically significant impairment, e.g., in social, academic, or occupational functioning, and be present in two or more settings, e.g., school (or work) and at home. The symptoms must not be better accounted for by another mental disorder. For the Inattentive Type, at least six of the following symptoms must have persisted for at least 6 months: lack of attention to details/careless mistakes; lack of sustained attention; poor listener; failure to follow through on tasks; poor organization; avoids tasks requiring sustained mental effort; loses things; easily distracted; forgetful. For the Hyperactive-Impulsive Type, at least six of the following symptoms must have persisted for at least 6 months: fidgeting/squirming; leaving seat; inappropriate running/climbing; difficulty with quiet activities; "on the go;" excessive talking; blurting answers; can't wait turn; intrusive. The Combined Type requires both inattentive and hyperactive-impulsive criteria to be met.

1.1 Special Diagnostic Considerations

Specific etiology of this syndrome is unknown, and there is no single diagnostic test. Adequate diagnosis requires the use of medical and special psychological, educational, and social resources. Learning may or may not be impaired. The diagnosis must be based upon a complete history and evaluation of the patient and not solely on the presence of the required number of DSM-IV characteristics.

1.2 Need for Comprehensive Treatment Program

CONCERTA® is indicated as an integral part of a total treatment program for ADHD that may include other measures (psychological, educational, social). Drug treatment may not be indicated for all patients with ADHD. Stimulants are not intended for use in patients who exhibit symptoms secondary to environmental factors and/or other primary psychiatric disorders, including psychosis. Appropriate educational placement is essential and psychosocial intervention is often helpful. When remedial measures alone are insufficient, the decision to prescribe stimulant medication will depend upon the physician's assessment of the chronicity and severity of the patient's symptoms.

2 DOSAGE AND ADMINISTRATION

2.1 General Dosing Information

CONCERTA® should be administered orally once daily in the morning with or without food.

CONCERTA® must be swallowed whole with the aid of liquids, and must not be chewed, divided, or crushed [see Patient Counseling Information (17)].

2.2 Patients New to Methylphenidate

The recommended starting dose of CONCERTA® for patients who are not currently taking methylphenidate or stimulants other than methylphenidate is 18 mg once daily for children and adolescents and 18 or 36 mg once daily for adults (see Table 1).

TABLE 1. CONCERTA® Recommended Starting Doses and Dose Ranges
Patient Age | Recommended Starting Dose | Dose Range
Children 6–12 years of age | 18 mg/day | 18 mg – 54 mg/day
Adolescents 13–17 years of age | 18 mg/day | 18 mg – 72 mg/day not to exceed 2 mg/kg/day
Adults 18–65 years of age | 18 or 36 mg/day | 18 mg – 72 mg/day

2.3 Patients Currently Using Methylphenidate

The recommended dose of CONCERTA® for patients who are currently taking methylphenidate twice daily or three times daily at doses of 10 to 60 mg/day is provided in Table 2. Dosing recommendations are based on current dose regimen and clinical judgment. Conversion dosage should not exceed 72 mg daily.

TABLE 2. Recommended Dose Conversion from Methylphenidate Regimens to CONCERTA®
Previous Methylphenidate Daily Dose | Recommended CONCERTA® Starting Dose
5 mg Methylphenidate twice daily or three times daily | 18 mg every morning
10 mg Methylphenidate twice daily or three times daily | 36 mg every morning
15 mg Methylphenidate twice daily or three times daily | 54 mg every morning
20 mg Methylphenidate twice daily or three times daily | 72 mg every morning

Other methylphenidate regimens: Clinical judgment should be used when selecting the starting dose.

2.4 Dose Titration

Doses may be increased in 18-mg increments at weekly intervals for patients who have not achieved an optimal response at a lower dose. Daily dosages above 54 mg in children and 72 mg in adolescents have not been studied and are not recommended. Daily dosages above 72 mg in adults are not recommended.

A 27-mg dosage strength is available for physicians who wish to prescribe between the 18-mg and 36-mg dosages.

2.5 Maintenance/Extended Treatment

There is no body of evidence available from controlled trials to indicate how long the patient with ADHD should be treated with CONCERTA®. It is generally agreed, however, that pharmacological treatment of ADHD may be needed for extended periods.

The effectiveness of CONCERTA® for long-term use, i.e., for more than 7 weeks, has not been systematically evaluated in controlled trials. The physician who elects to use CONCERTA® for extended periods in patients with ADHD should periodically re-evaluate the long-term usefulness of the drug for the individual patient with trials off medication to assess the patient's functioning without pharmacotherapy. Improvement may be sustained when the drug is either temporarily or permanently discontinued.

2.6 Dose Reduction and Discontinuation

If paradoxical aggravation of symptoms or other adverse events occur, the dosage should be reduced, or, if necessary, the drug should be discontinued.

If improvement is not observed after appropriate dosage adjustment over a one-month period, the drug should be discontinued.

3 DOSAGE FORMS AND STRENGTHS

CONCERTA® (methylphenidate HCl) Extended-Release Tablets are available in the following dosage strengths: 18-mg tablets are yellow and imprinted with "alza 18," 27-mg tablets are gray and imprinted with "alza 27," 36-mg tablets are white and imprinted with "alza 36," and 54-mg tablets are brownish-red and imprinted with "alza 54."

4 CONTRAINDICATIONS

4.1 Hypersensitivity to Methylphenidate

Hypersensitivity reactions, such as angioedema and anaphylactic reactions, have been observed in patients treated with CONCERTA®. Therefore, CONCERTA® is contraindicated in patients known to be hypersensitive to methylphenidate or other components of the product [see Adverse Reactions (6.6)].

4.2 Agitation

CONCERTA® is contraindicated in patients with marked anxiety, tension, and agitation, since the drug may aggravate these symptoms.

4.3 Glaucoma

CONCERTA® is contraindicated in patients with glaucoma.

4.4 Tics

CONCERTA® is contraindicated in patients with motor tics or with a family history or diagnosis of Tourette's syndrome [see Adverse Reactions (6.4)].

4.5 Monoamine Oxidase Inhibitors

CONCERTA® is contraindicated during treatment with monoamine oxidase (MAO) inhibitors, and also within a minimum of 14 days following discontinuation of a MAO inhibitor (hypertensive crises may result) [see Drug Interactions (7.1)].

5 WARNINGS AND PRECAUTIONS

5.1 Serious Cardiovascular Events

Sudden Death and Preexisting Structural Cardiac Abnormalities or Other Serious Heart Problems

Children and Adolescents

Sudden death has been reported in association with CNS stimulant treatment at usual doses in children and adolescents with structural cardiac abnormalities or other serious heart problems. Although some serious heart problems alone carry an increased risk of sudden death, stimulant products generally should not be used in children or adolescents with known serious structural cardiac abnormalities, cardiomyopathy, serious heart rhythm abnormalities, or other serious cardiac problems that may place them at increased vulnerability to the sympathomimetic effects of a stimulant drug.

Adults

Sudden deaths, stroke, and myocardial infarction have been reported in adults taking stimulant drugs at usual doses for ADHD. Although the role of stimulants in these adult cases is also unknown, adults have a greater likelihood than children of having serious structural cardiac abnormalities, cardiomyopathy, serious heart rhythm abnormalities, coronary artery disease, or other serious cardiac problems. Adults with such abnormalities should also generally not be treated with stimulant drugs.

Hypertension and Other Cardiovascular Conditions

Stimulant medications cause a modest increase in average blood pressure (about 2 to 4 mm Hg) and average heart rate (about 3 to 6 bpm) [see Adverse Reactions (6.5)], and individuals may have larger increases. While the mean changes alone would not be expected to have short-term consequences, all patients should be monitored for larger changes in heart rate and blood pressure. Caution is indicated in treating patients whose underlying medical conditions might be compromised by increases in blood pressure or heart rate, e.g., those with preexisting hypertension, heart failure, recent myocardial infarction, or ventricular arrhythmia.

Assessing Cardiovascular Status in Patients Being Treated with Stimulant Medications

Children, adolescents, or adults who are being considered for treatment with stimulant medications should have a careful history (including assessment for a family history of sudden death or ventricular arrhythmia) and physical exam to assess for the presence of cardiac disease, and should receive further cardiac evaluation if findings suggest such disease (e.g., electrocardiogram and echocardiogram). Patients who develop symptoms such as exertional chest pain, unexplained syncope, or other symptoms suggestive of cardiac disease during stimulant treatment should undergo a prompt cardiac evaluation.

5.2 Psychiatric Adverse Events

Preexisting Psychosis

Administration of stimulants may exacerbate symptoms of behavior disturbance and thought disorder in patients with a preexisting psychotic disorder.

Bipolar Illness

Particular care should be taken in using stimulants to treat ADHD in patients with comorbid bipolar disorder because of concern for possible induction of a mixed/manic episode in such patients. Prior to initiating treatment with a stimulant, patients with comorbid depressive symptoms should be adequately screened to determine if they are at risk for bipolar disorder; such screening should include a detailed psychiatric history, including a family history of suicide, bipolar disorder, and depression.

Emergence of New Psychotic or Manic Symptoms

Treatment-emergent psychotic or manic symptoms, e.g., hallucinations, delusional thinking, or mania in patients without a prior history of psychotic illness or mania can be caused by stimulants at usual doses. If such symptoms occur, consideration should be given to a possible causal role of the stimulant, and discontinuation of treatment may be appropriate. In a pooled analysis of multiple short-term, placebo-controlled studies, such symptoms occurred in about 0.1% (4 patients with events out of 3482 exposed to methylphenidate or amphetamine for several weeks at usual doses) of stimulant-treated patients compared to 0 in placebo-treated patients.

Aggression

Aggressive behavior or hostility is often observed in patients with ADHD, and has been reported in clinical trials and the postmarketing experience of some medications indicated for the treatment of ADHD. Although there is no systematic evidence that stimulants cause aggressive behavior or hostility, patients beginning treatment for ADHD should be monitored for the appearance of or worsening of aggressive behavior or hostility.

5.3 Seizures

There is some clinical evidence that stimulants may lower the convulsive threshold in patients with prior history of seizures, in patients with prior EEG abnormalities in absence of seizures, and, very rarely, in patients without a history of seizures and no prior EEG evidence of seizures. In the presence of seizures, the drug should be discontinued.

5.4 Long-Term Suppression of Growth

Careful follow-up of weight and height in children ages 7 to 10 years who were randomized to either methylphenidate or nonmedication treatment groups over 14 months, as well as in naturalistic subgroups of newly methylphenidate-treated and nonmedication-treated children over 36 months (to the ages of 10 to 13 years), suggests that consistently medicated children (i.e., treatment for 7 days per week throughout the year) have a temporary slowing in growth rate (on average, a total of about 2 cm less growth in height and 2.7 kg less growth in weight over 3 years), without evidence of growth rebound during this period of development. Published data are inadequate to determine whether chronic use of amphetamines may cause similar suppression of growth; however, it is anticipated that they likely have this effect as well. Therefore, growth should be monitored during treatment with stimulants, and patients who are not growing or gaining height or weight as expected may need to have their treatment interrupted.

5.5 Visual Disturbance

Difficulties with accommodation and blurring of vision have been reported with stimulant treatment.

5.6 Potential for Gastrointestinal Obstruction

Because the CONCERTA® tablet is nondeformable and does not appreciably change in shape in the GI tract, CONCERTA® should not ordinarily be administered to patients with preexisting severe gastrointestinal narrowing (pathologic or iatrogenic, for example: esophageal motility disorders, small bowel inflammatory disease, "short gut" syndrome due to adhesions or decreased transit time, past history of peritonitis, cystic fibrosis, chronic intestinal pseudoobstruction, or Meckel's diverticulum). There have been rare reports of obstructive symptoms in patients with known strictures in association with the ingestion of drugs in nondeformable controlled-release formulations. Due to the controlled-release design of the tablet, CONCERTA® should be used only in patients who are able to swallow the tablet whole [see Patient Counseling Information (17)].

5.7 Hematologic Monitoring

Periodic CBC, differential, and platelet counts are advised during prolonged therapy.

6 ADVERSE REACTIONS

The following are discussed in more detail in other sections of the labeling:

- Drug Dependence [see Box Warning]
- Hypersensitivity to Methylphenidate [see Contraindications (4.1)]
- Agitation [see Contraindications (4.2)]
- Glaucoma [see Contraindications (4.3)]
- Tics [see Contraindications (4.4)]
- Monoamine Oxidase Inhibitors [see Contraindications (4.5) and Drug Interactions (7.1)]
- Serious Cardiovascular Events [see Warnings and Precautions (5.1)]
- Psychiatric Adverse Events [see Warnings and Precautions (5.2)]
- Seizures [see Warnings and Precautions (5.3)]
- Long-Term Suppression of Growth [see Warnings and Precautions (5.4)]
- Visual Disturbance [see Warnings and Precautions (5.5)]
- Potential for Gastrointestinal Obstruction [see Warnings and Precautions (5.6)]
- Hematologic Monitoring [see Warnings and Precautions (5.7)]

The most common adverse reaction in double-blind clinical trials (>5%) in pediatric patients (children and adolescents) was abdominal pain upper. The most common adverse reactions in double-blind clinical trials (>5%) in adult patients were decreased appetite, headache, dry mouth, nausea, insomnia, anxiety, dizziness, weight decreased, irritability, and hyperhidrosis [see Adverse Reactions (6.1)].

The most common adverse reactions associated with discontinuation (≥1%) from either pediatric or adult clinical trials were anxiety, irritability, insomnia, and blood pressure increased [see Adverse Reactions (6.3)].

The development program for CONCERTA® included exposures in a total of 3906 participants in clinical trials. Children, adolescents, and adults with ADHD were evaluated in 6 controlled clinical studies and 11 open-label clinical studies (see Table 3). Safety was assessed by collecting adverse events, vital signs, weights, and ECGs, and by performing physical examinations and laboratory analyses.

Table 3. CONCERTA® Exposure in Double-Blind and Open-Label Clinical Studies
Patient Population | N | Dose Range
Children | 2216 | 18 to 54 mg once daily
Adolescents | 502 | 18 to 72 mg once daily
Adults | 1188 | 18 to 108 mg once daily

Adverse events during exposure were obtained primarily by general inquiry and recorded by clinical investigators using their own terminology. Consequently, to provide a meaningful estimate of the proportion of individuals experiencing adverse events, events were grouped in standardized categories using MedDRA terminology.

The stated frequencies of adverse events represent the proportion of individuals who experienced, at least once, a treatment-emergent adverse event of the type listed. An event was considered treatment-emergent if it occurred for the first time or worsened while receiving therapy following baseline evaluation.

Throughout this section, adverse reactions are reported. Adverse reactions are adverse events that were considered to be reasonably associated with the use of CONCERTA® based on the comprehensive assessment of the available adverse event information. A causal association for CONCERTA® often cannot be reliably established in individual cases. Further, because clinical trials are conducted under widely varying conditions, adverse reaction rates observed in the clinical trials of a drug cannot be directly compared to rates in clinical trials of another drug and may not reflect the rates observed in clinical practice.

The majority of adverse reactions were mild to moderate in severity.

6.1 Commonly Observed Adverse Reactions in Double-Blind, Placebo-Controlled Clinical Trials

Adverse reactions in either the pediatric or adult double-blind adverse reactions tables may be relevant for both patient populations.

Children and Adolescents

Table 4 lists the adverse reactions reported in 1% or more of CONCERTA®-treated children and adolescent subjects in 4 placebo-controlled, double-blind clinical trials.

Table 4. Adverse Reactions Reported by ≥1% of CONCERTA®-Treated Children and Adolescent Subjects in 4 Placebo-Controlled, Double-Blind Clinical Trials of CONCERTA®
System/Organ Class Adverse Reaction | CONCERTA® (n=321) % | Placebo (n=318) %
Gastrointestinal Disorders
Abdominal pain upper | 6.2 | 3.8
Vomiting | 2.8 | 1.6
General Disorders and Administration Site Conditions
Pyrexia | 2.2 | 0.9
Infections and Infestations
Nasopharyngitis | 2.8 | 2.2
Nervous System Disorders
Dizziness | 1.9 | 0
Psychiatric Disorders
Insomnia [Terms of Initial insomnia (CONCERTA®=0.6%) and Insomnia (CONCERTA®=2.2%) are combined into Insomnia.] | 2.8 | 0.3
Respiratory, Thoracic and Mediastinal Disorders
Cough | 1.9 | 0.9
Oropharyngeal pain | 1.2 | 0.9

The majority of adverse reactions were mild to moderate in severity.

Adults

Table 5 lists the adverse reactions reported in 1% or more of CONCERTA®-treated adults in 2 placebo-controlled, double-blind clinical trials.

Table 5. Adverse Reactions Reported by ≥1% of CONCERTA®-Treated Adult Subjects in 2 Placebo-Controlled, Double-Blind Clinical Trials [Included doses up to 108 mg.]
System/Organ Class Adverse Reaction | CONCERTA® (n=415) % | Placebo (n=212) %
Cardiac Disorders
Tachycardia | 4.8 | 0
Palpitations | 3.1 | 0.9
Ear and Labyrinth Disorders
Vertigo | 1.7 | 0
Eye Disorders
Vision blurred | 1.7 | 0.5
Gastrointestinal Disorders
Dry mouth | 14.0 | 3.8
Nausea | 12.8 | 3.3
Dyspepsia | 2.2 | 0.9
Vomiting | 1.7 | 0.5
Constipation | 1.4 | 0.9
General Disorders and Administration Site Conditions
Irritability | 5.8 | 1.4
Infections and Infestations
Upper respiratory tract infection | 2.2 | 0.9
Investigations
Weight decreased | 6.5 | 3.3
Metabolism and Nutrition Disorders
Decreased appetite | 25.3 | 6.6
Anorexia | 1.7 | 0
Musculoskeletal and Connective Tissue Disorders
Muscle tightness | 1.9 | 0
Nervous System Disorders
Headache | 22.2 | 15.6
Dizziness | 6.7 | 5.2
Tremor | 2.7 | 0.5
Paresthesia | 1.2 | 0
Sedation | 1.2 | 0
Tension headache | 1.2 | 0.5
Psychiatric Disorders
Insomnia | 12.3 | 6.1
Anxiety | 8.2 | 2.4
Initial insomnia | 4.3 | 2.8
Depressed mood | 3.9 | 1.4
Nervousness | 3.1 | 0.5
Restlessness | 3.1 | 0
Agitation | 2.2 | 0.5
Aggression | 1.7 | 0.5
Bruxism | 1.7 | 0.5
Depression | 1.7 | 0.9
Libido decreased | 1.7 | 0.5
Affect lability | 1.4 | 0.9
Confusional state | 1.2 | 0.5
Tension | 1.2 | 0.5
Respiratory, Thoracic and Mediastinal Disorders
Oropharyngeal pain | 1.7 | 1.4
Skin and Subcutaneous Tissue Disorders
Hyperhidrosis | 5.1 | 0.9

The majority of ADRs were mild to moderate in severity.

6.2 Other Adverse Reactions Observed in CONCERTA® Clinical Trials

This section includes adverse reactions reported by CONCERTA®-treated subjects in double-blind trials that do not meet the criteria specified for Table 4 or Table 5 and all adverse reactions reported by CONCERTA®-treated subjects who participated in open-label and postmarketing clinical trials.

Blood and Lymphatic System Disorders: Leukopenia

Eye Disorders: Accommodation disorder, Dry eye

Vascular Disorders: Hot flush

Gastrointestinal Disorders: Abdominal discomfort, Abdominal pain, Diarrhea

General Disorders and Administrative Site Conditions: Asthenia, Fatigue, Feeling jittery, Thirst

Infections and Infestations: Sinusitis

Investigations: Alanine aminotransferase increased, Blood pressure increased, Cardiac murmur, Heart rate increased

Musculoskeletal and Connective Tissue Disorders: Muscle spasms

Nervous System Disorders: Lethargy, Psychomotor hyperactivity, Somnolence

Psychiatric Disorders: Anger, Hypervigilance, Mood altered, Mood swings, Panic attack, Sleep disorder, Tearfulness, Tic

Reproductive System and Breast Disorders: Erectile dysfunction

Respiratory, Thoracic and Mediastinal Disorders: Dyspnea

Skin and Subcutaneous Tissue Disorders: Rash, Rash macular

Vascular Disorders: Hypertension

6.3 Discontinuation Due to Adverse Reactions

Adverse reactions in the 4 placebo-controlled studies of children and adolescents leading to discontinuation occurred in 2 CONCERTA® patients (0.6%) including depressed mood (1, 0.3%) and headache and insomnia (1, 0.3%), and 6 placebo patients (1.9%) including headache and insomnia (1, 0.3%), irritability (2, 0.6%), headache (1, 0.3%), psychomotor hyperactivity (1, 0.3%), and tic (1, 0.3%).

In the 2 placebo-controlled studies of adults, 25 CONCERTA® patients (6.0%) and 6 placebo patients (2.8%) discontinued due to an adverse reaction. Those events with an incidence of >0.5% in the CONCERTA® patients included anxiety (1.7%), irritability (1.4%), blood pressure increased (1.0%), and nervousness (0.7%). In placebo patients, blood pressure increased and depressed mood had an incidence of >0.5% (0.9%).

In the 11 open-label studies of children, adolescents, and adults, 266 CONCERTA® patients (7.0%) discontinued due to an adverse reaction. Those events with an incidence of >0.5% included insomnia (1.2%), irritability (0.8%), anxiety (0.7%), decreased appetite (0.7%), and tic (0.6%).

6.4 Tics

In a long-term uncontrolled study (n=432 children), the cumulative incidence of new onset of tics was 9% after 27 months of treatment with CONCERTA®.

In a second uncontrolled study (n=682 children) the cumulative incidence of new-onset tics was 1% (9/682 children). The treatment period was up to 9 months with mean treatment duration of 7.2 months.

6.5 Blood Pressure and Heart Rate Increases

In the laboratory classroom clinical trials in children (Studies 1 and 2), both CONCERTA® once daily and methylphenidate three times daily increased resting pulse by an average of 2 to 6 bpm and produced average increases of systolic and diastolic blood pressure of roughly 1 to 4 mm Hg during the day, relative to placebo. In the placebo-controlled adolescent trial (Study 4), mean increases from baseline in resting pulse rate were observed with CONCERTA® and placebo at the end of the double-blind phase (5 and 3 beats/minute, respectively). Mean increases from baseline in blood pressure at the end of the double-blind phase for CONCERTA® and placebo-treated patients were 0.7 and 0.7 mm Hg (systolic) and 2.6 and 1.4 mm Hg (diastolic), respectively. In one placebo-controlled study in adults (Study 6), dose-dependent mean increases of 3.9 to 9.8 bpm from baseline in standing pulse rate were observed with CONCERTA® at the end of the double-blind treatment vs. an increase of 2.7 beats/minute with placebo. Mean changes from baseline in standing blood pressure at the end of double-blind treatment ranged from 0.1 to 2.2 mm Hg (systolic) and -0.7 to 2.2 mm Hg (diastolic) for CONCERTA® and was 1.1 mm Hg (systolic) and -1.8 mm Hg (diastolic) for placebo. In a second placebo-controlled study in adults (Study 5), mean changes from baseline in resting pulse rate were observed for CONCERTA® and placebo at the end of the double-blind treatment (3.6 and –1.6 beats/minute, respectively). Mean changes from baseline in blood pressure at the end of the double–blind treatment for CONCERTA® and placebo-treated patients were –1.2 and –0.5 mm Hg (systolic) and 1.1 and 0.4 mm Hg (diastolic), respectively [see Warnings and Precautions (5.1]).

6.6 Postmarketing Experience

The following additional adverse reactions have been identified during postapproval use of CONCERTA®. Because these reactions are reported voluntarily from a population of uncertain size, it is not always possible to reliably estimate their frequency:

Blood and Lymphatic System Disorders: Pancytopenia, Thrombocytopenia, Thrombocytopenic purpura

Cardiac Disorders: Angina pectoris, Bradycardia, Extrasystoles, Supraventricular tachycardia, Ventricular extrasystoles

Eye Disorders: Diplopia, Mydriasis, Visual impairment

General Disorders: Chest pain, Chest discomfort, Drug effect decreased, Hyperpyrexia, Therapeutic response decreased

Immune System Disorders: Hypersensitivity reactions such as Angioedema, Anaphylactic reactions, Auricular swelling, Bullous conditions, Exfoliative conditions, Urticarias, Pruritus NEC, Rashes, Eruptions, and Exanthemas NEC

Investigations: Blood alkaline phosphatase increased, Blood bilirubin increased, Hepatic enzyme increased, Platelet count decreased, White blood cell count abnormal

Musculoskeletal, Connective Tissue and Bone Disorders: Arthralgia, Myalgia, Muscle twitching

Nervous System Disorders: Convulsion, Grand mal convulsion, Dyskinesia

Psychiatric Disorders: Disorientation, Hallucination, Hallucination auditory, Hallucination visual, Mania

Skin and Subcutaneous Tissue Disorders: Alopecia, Erythema

Vascular Disorders: Raynaud's phenomenon

7 DRUG INTERACTIONS

7.1 MAO Inhibitors

CONCERTA® should not be used in patients being treated (currently or within the preceding 2 weeks) with MAO inhibitors [see Contraindications (4.5)].

7.2 Vasopressor Agents

Because of possible increases in blood pressure, CONCERTA® should be used cautiously with vasopressor agents [see Warnings and Precautions (5.1)].

7.3 Coumarin Anticoagulants, Antidepressants, and Selective Serotonin Reuptake Inhibitors

Human pharmacologic studies have shown that methylphenidate may inhibit the metabolism of coumarin anticoagulants, anticonvulsants (eg, phenobarbital, phenytoin, primidone), and some antidepressants (tricyclics and selective serotonin reuptake inhibitors). Downward dose adjustment of these drugs may be required when given concomitantly with methylphenidate. It may be necessary to adjust the dosage and monitor plasma drug concentrations (or, in the case of coumarin, coagulation times), when initiating or discontinuing concomitant methylphenidate.

8 USE IN SPECIFIC POPULATIONS

8.1 Pregnancy

TERATOGENIC EFFECTS

Pregnancy Category C

Methylphenidate has been shown to have teratogenic effects in rabbits when given in doses of 200 mg/kg/day, which is approximately 100 times and 40 times the maximum recommended human dose on a mg/kg and mg/m^2 basis, respectively.

A reproduction study in rats revealed no evidence of harm to the fetus at oral doses up to 30 mg/kg/day, approximately 15-fold and 3-fold the maximum recommended human dose of CONCERTA® on a mg/kg and mg/m^2 basis, respectively. The approximate plasma exposure to methylphenidate plus its main metabolite PPAA in pregnant rats was 1–2 times that seen in trials in volunteers and patients with the maximum recommended dose of CONCERTA® based on the AUC.

The safety of methylphenidate for use during human pregnancy has not been established. There are no adequate and well-controlled studies in pregnant women. CONCERTA® should be used during pregnancy only if the potential benefit justifies the potential risk to the fetus.

8.2 Labor and Delivery

The effect of CONCERTA® on labor and delivery in humans is unknown.

8.3 Nursing Mothers

It is not known whether methylphenidate is excreted in human milk. Because many drugs are excreted in human milk, caution should be exercised if CONCERTA® is administered to a nursing woman.

In lactating female rats treated with a single oral dose of 5 mg/kg radiolabeled methylphenidate, radioactivity (representing methylphenidate and/or its metabolites) was observed in milk and levels were generally similar to those in plasma.

8.4 Pediatric Use

CONCERTA® should not be used in children under six years, since safety and efficacy in this age group have not been established. Long-term effects of methylphenidate in children have not been well established.

8.5 Geriatric Use

CONCERTA® has not been studied in patients greater than 65 years of age.

9 DRUG ABUSE AND DEPENDENCE

9.1 Controlled Substance

Methylphenidate is a Schedule II controlled substance under the Controlled Substances Act.

9.2 Abuse

As noted in the Box Warning, CONCERTA® should be given cautiously to patients with a history of drug dependence or alcoholism. Chronic abusive use can lead to marked tolerance and psychological dependence with varying degrees of abnormal behavior. Frank psychotic episodes can occur, especially with parenteral abuse.

In two placebo-controlled human abuse potential studies, single oral doses of CONCERTA® were compared to single oral doses of immediate-release methylphenidate (IR MPH) and placebo in subjects with a history of recreational stimulant use to assess relative abuse potential. For the purpose of this assessment, the response for each of the subjective measures was defined as the maximum effect within the first 8 hours after dose administration.

In one study (n=40), both CONCERTA® (108 mg) and 60 mg IR MPH compared to placebo produced statistically significantly greater responses on the five subjective measures suggestive of abuse potential. In comparisons between the two active treatments, however, CONCERTA® (108 mg) produced variable responses on positive subjective measures that were either statistically indistinguishable from (Abuse Potential, Drug Liking, Amphetamine, and Morphine Benzedrine Group [Euphoria]) or statistically less than (Stimulation – Euphoria) responses produced by 60 mg IR MPH.

In another study (n=49), both doses of CONCERTA® (54 mg and 108 mg) and both doses of IR MPH (50 mg and 90 mg) produced statistically significantly greater responses compared to placebo on the two primary scales used in the study (Drug Liking, Euphoria). When doses of CONCERTA® (54 mg and 108 mg) were compared to IR MPH (50 mg and 90 mg), respectively, CONCERTA® produced statistically significantly lower subjective responses on these two scales than IR MPH. CONCERTA® (108 mg) produced responses that were statistically indistinguishable from the responses on these two scales produced by IR MPH (50 mg). Differences in subjective responses to the respective doses should be considered in the context that only 22% of the total amount of methylphenidate in CONCERTA® tablets is available for immediate release from the drug overcoat [see System Components and Performance (11.1)].

Although these findings reveal a relatively lower response to CONCERTA® on subjective measures suggestive of abuse potential compared to IR MPH at roughly equivalent total MPH doses, the relevance of these findings to the abuse potential of CONCERTA® in the community is unknown.

9.3 Dependence

As noted in the Box Warning, careful supervision is required during withdrawal from abusive use since severe depression may occur. Withdrawal following chronic therapeutic use may unmask symptoms of the underlying disorder that may require follow-up.

10 OVERDOSAGE

10.1 Signs and Symptoms

Signs and symptoms of CONCERTA® overdosage, resulting principally from overstimulation of the CNS and from excessive sympathomimetic effects, may include the following: vomiting, agitation, muscle twitching, convulsion, grand mal convulsion, confusional state, hallucinations (auditory and/or visual), hyperhidrosis, headache, pyrexia, tachycardia, palpitations, heart rate increased, sinus arrhythmia, hypertension, mydriasis, and dry mouth.

10.2 Recommended Treatment

Treatment consists of appropriate supportive measures. The patient must be protected against self-injury and against external stimuli that would aggravate overstimulation already present. Gastric contents may be evacuated by gastric lavage as indicated. Before performing gastric lavage, control agitation and seizures if present and protect the airway. Other measures to detoxify the gut include administration of activated charcoal and a cathartic. Intensive care must be provided to maintain adequate circulation and respiratory exchange; external cooling procedures may be required for pyrexia.

Efficacy of peritoneal dialysis or extracorporeal hemodialysis for CONCERTA® overdosage has not been established.

The prolonged release of methylphenidate from CONCERTA® should be considered when treating patients with overdose.

10.3 Poison Control Center

As with the management of all overdosage, the possibility of multiple-drug ingestion should be considered. The physician may wish to consider contacting a poison control center for up-to-date information on the management of overdosage with methylphenidate.

11 DESCRIPTION

CONCERTA® is a central nervous system (CNS) stimulant. CONCERTA® is available in four tablet strengths. Each extended-release tablet for once-a-day oral administration contains 18, 27, 36, or 54 mg of methylphenidate HCl USP and is designed to have a 12-hour duration of effect. Chemically, methylphenidate HCl is d,l (racemic) methyl α-phenyl-2-piperidineacetate hydrochloride. Its empirical formula is C14H19NO2•HCl. Its structural formula is:

Methylphenidate HCl USP is a white, odorless crystalline powder. Its solutions are acid to litmus. It is freely soluble in water and in methanol, soluble in alcohol, and slightly soluble in chloroform and in acetone. Its molecular weight is 269.77.

CONCERTA® also contains the following inert ingredients: butylated hydroxytoluene, carnauba wax, cellulose acetate, hypromellose, lactose, phosphoric acid, poloxamer, polyethylene glycol, polyethylene oxides, povidone, propylene glycol, sodium chloride, stearic acid, succinic acid, synthetic iron oxides, titanium dioxide, and triacetin.

11.1 System Components and Performance

CONCERTA® uses osmotic pressure to deliver methylphenidate HCl at a controlled rate. The system, which resembles a conventional tablet in appearance, comprises an osmotically active trilayer core surrounded by a semipermeable membrane with an immediate-release drug overcoat. The trilayer core is composed of two drug layers containing the drug and excipients, and a push layer containing osmotically active components. There is a precision-laser drilled orifice on the drug-layer end of the tablet. In an aqueous environment, such as the gastrointestinal tract, the drug overcoat dissolves within one hour, providing an initial dose of methylphenidate. Water permeates through the membrane into the tablet core. As the osmotically active polymer excipients expand, methylphenidate is released through the orifice. The membrane controls the rate at which water enters the tablet core, which in turn controls drug delivery. Furthermore, the drug release rate from the system increases with time over a period of 6 to 7 hours due to the drug-concentration gradient incorporated into the two drug layers of CONCERTA®. The biologically inert components of the tablet remain intact during gastrointestinal transit and are eliminated in the stool as a tablet shell along with insoluble core components. It is possible that CONCERTA® extended-release tablets may be visible on abdominal x-rays under certain circumstances, especially when digital enhancing techniques are utilized.

12 CLINICAL PHARMACOLOGY

12.1 Mechanism of Action

Methylphenidate HCl is a central nervous system (CNS) stimulant. The mode of therapeutic action in Attention Deficit Hyperactivity Disorder (ADHD) is not known. Methylphenidate is thought to block the reuptake of norepinephrine and dopamine into the presynaptic neuron and increase the release of these monoamines into the extraneuronal space.

12.2 Pharmacodynamics

Methylphenidate is a racemic mixture comprised of the d- and l-isomers. The d-isomer is more pharmacologically active than the l-isomer.

12.3 Pharmacokinetics

Absorption

Methylphenidate is readily absorbed. Following oral administration of CONCERTA®, plasma methylphenidate concentrations increase rapidly, reaching an initial maximum at about 1 hour, followed by gradual ascending concentrations over the next 5 to 9 hours, after which a gradual decrease begins. Mean times to reach peak plasma concentrations across all doses of CONCERTA® occurred between 6 and 10 hours.

CONCERTA® once daily minimizes the fluctuations between peak and trough concentrations associated with immediate-release methylphenidate three times daily (see Figure 1). The relative bioavailability of CONCERTA® once daily and methylphenidate three times daily in adults is comparable.

Figure 1. Mean methylphenidate plasma concentrations in 36 adults, following a single dose of CONCERTA® 18 mg once daily and immediate-release methylphenidate 5 mg three times daily administered every 4 hours.

The mean single-dose pharmacokinetic parameters in 36 healthy adults following the administration of CONCERTA® 18 mg once daily and methylphenidate 5 mg three times daily are summarized in Table 6.

TABLE 6. Pharmacokinetic Parameters (Mean ± SD) After Single Dose in Healthy Adults
Parameters | CONCERTA® (18 mg once daily) (n=36) | Methylphenidate (5 mg three times daily) (n=35)
Cmax (ng/mL) | 3.7 ± 1.0 | 4.2 ± 1.0
Tmax (h) | 6.8 ± 1.8 | 6.5 ± 1.8
AUCinf (ng∙h/mL) | 41.8 ± 13.9 | 38.0 ± 11.0
t½ (h) | 3.5 ± 0.4 | 3.0 ± 0.5

The pharmacokinetics of CONCERTA® were evaluated in healthy adults following single- and multiple-dose administration (steady state) of doses up to 144 mg/day. The mean half-life was about 3.6 hours. No differences in the pharmacokinetics of CONCERTA® were noted following single and repeated once-daily dosing, indicating no significant drug accumulation. The AUC and t1/2 following repeated once-daily dosing are similar to those following the first dose of CONCERTA® in a dose range of 18 to 144 mg.

Dose Proportionality

Following administration of CONCERTA® in single doses of 18, 36, and 54 mg/day to healthy adults, Cmax and AUC (0–inf) of d-methylphenidate were proportional to dose, whereas l-methylphenidate Cmax and AUC (0–inf) increased disproportionately with respect to dose. Following administration of CONCERTA®, plasma concentrations of the l-isomer were approximately 1/40 the plasma concentrations of the d-isomer.

In healthy adults, single and multiple dosing of once-daily CONCERTA® doses from 54 to 144 mg/day resulted in linear and dose-proportional increases in Cmax and AUCinf for total methylphenidate (MPH) and its major metabolite, α-phenyl-piperidine acetic acid (PPAA). There was no time dependency in the pharmacokinetics of methylphenidate. The ratio of metabolite (PPAA) to parent drug (MPH) was constant across doses from 54 to 144 mg/day, both after single dose and upon multiple dosing.

In a multiple-dose study in adolescent ADHD patients aged 13 to 16 administered their prescribed dose (18 to 72 mg/day) of CONCERTA®, mean Cmax and AUCTAU of d- and total methylphenidate increased proportionally with respect to dose.

Distribution

Plasma methylphenidate concentrations in adults and adolescents decline biexponentially following oral administration. The half-life of methylphenidate in adults and adolescents following oral administration of CONCERTA® was approximately 3.5 hours.

Metabolism and Excretion

In humans, methylphenidate is metabolized primarily by de-esterification to PPAA, which has little or no pharmacologic activity. In adults the metabolism of CONCERTA® once daily as evaluated by metabolism to PPAA is similar to that of methylphenidate three times daily. The metabolism of single and repeated once-daily doses of CONCERTA® is similar.

After oral dosing of radiolabeled methylphenidate in humans, about 90% of the radioactivity was recovered in urine. The main urinary metabolite was PPAA, accounting for approximately 80% of the dose.

Food Effects

In patients, there were no differences in either the pharmacokinetics or the pharmacodynamic performance of CONCERTA® when administered after a high-fat breakfast. There is no evidence of dose dumping in the presence or absence of food.

Special Populations

Gender

In healthy adults, the mean dose-adjusted AUC (0–inf) values for CONCERTA® were 36.7 ng∙h/mL in men and 37.1 ng∙h/mL in women, with no differences noted between the two groups.

Race

In adults receiving CONCERTA®, dose-adjusted AUC (0–inf) was consistent across ethnic groups; however, the sample size may have been insufficient to detect ethnic variations in pharmacokinetics.

Age

Increase in age resulted in increased apparent oral clearance (CL/F) (58% increase in adolescents compared to children). Some of these differences could be explained by body-weight differences among these populations. This suggests that subjects with higher body weight may have lower exposures of total methylphenidate at similar doses.

The pharmacokinetics of CONCERTA® have not been studied in children less than 6 years of age.

Renal Insufficiency

There is no experience with the use of CONCERTA® in patients with renal insufficiency. After oral administration of radiolabeled methylphenidate in humans, methylphenidate was extensively metabolized and approximately 80% of the radioactivity was excreted in the urine in the form of PPAA. Since renal clearance is not an important route of methylphenidate clearance, renal insufficiency is expected to have little effect on the pharmacokinetics of CONCERTA®.

Hepatic Insufficiency

There is no experience with the use of CONCERTA® in patients with hepatic insufficiency.

13 NONCLINICAL TOXICOLOGY

13.1 Carcinogenesis, Mutagenesis, and Impairment of Fertility

Carcinogenesis

In a lifetime carcinogenicity study carried out in B6C3F1 mice, methylphenidate caused an increase in hepatocellular adenomas and, in males only, an increase in hepatoblastomas at a daily dose of approximately 60 mg/kg/day. This dose is approximately 30 times and 4 times the maximum recommended human dose of CONCERTA® on a mg/kg and mg/m^2 basis, respectively. Hepatoblastoma is a relatively rare rodent malignant tumor type. There was no increase in total malignant hepatic tumors. The mouse strain used is sensitive to the development of hepatic tumors, and the significance of these results to humans is unknown.

Methylphenidate did not cause any increases in tumors in a lifetime carcinogenicity study carried out in F344 rats; the highest dose used was approximately 45 mg/kg/day, which is approximately 22 times and 5 times the maximum recommended human dose of CONCERTA® on a mg/kg and mg/m^2 basis, respectively.

In a 24-week carcinogenicity study in the transgenic mouse strain p53+/-, which is sensitive to genotoxic carcinogens, there was no evidence of carcinogenicity. Male and female mice were fed diets containing the same concentration of methylphenidate as in the lifetime carcinogenicity study; the high-dose groups were exposed to 60 to 74 mg/kg/day of methylphenidate.

Mutagenesis

Methylphenidate was not mutagenic in the in vitro Ames reverse mutation assay or the in vitro mouse lymphoma cell forward mutation assay. Sister chromatid exchanges and chromosome aberrations were increased, indicative of a weak clastogenic response, in an in vitro assay in cultured Chinese Hamster Ovary cells. Methylphenidate was negative in vivo in males and females in the mouse bone marrow micronucleus assay.

Impairment of Fertility

Methylphenidate did not impair fertility in male or female mice that were fed diets containing the drug in an 18-week Continuous Breeding study. The study was conducted at doses up to 160 mg/kg/day, approximately 80-fold and 8-fold the highest recommended human dose of CONCERTA® on a mg/kg and mg/m^2 basis, respectively.

14 CLINICAL STUDIES

CONCERTA® was demonstrated to be effective in the treatment of Attention Deficit Hyperactivity Disorder (ADHD) in 4 randomized, double-blind, placebo-controlled studies in children and adolescents and 2 double-blind placebo-controlled studies in adults who met the Diagnostic and Statistical Manual 4th edition (DSM-IV) criteria for ADHD.

14.1 Children

Three double-blind, active- and placebo-controlled studies were conducted in 416 children aged 6 to 12 years. The controlled studies compared CONCERTA® given once daily (18, 36, or 54 mg), methylphenidate given three times daily over 12 hours (15, 30, or 45 mg total daily dose), and placebo in two single-center, 3-week crossover studies (Studies 1 and 2) and in a multicenter, 4-week, parallel-group comparison (Study 3). The primary comparison of interest in all three trials was CONCERTA® versus placebo.

Symptoms of ADHD were evaluated by community schoolteachers using the Inattention / Overactivity with Aggression (IOWA) Conners scale. Statistically significant reduction in the Inattention / Overactivity subscale versus placebo was shown consistently across all three controlled studies for CONCERTA®. The scores for CONCERTA® and placebo for the three studies are presented in Figure 2.

Figure 2: Mean Community School Teacher IOWA Conners Inattention/Overactivity Scores with CONCERTA® once daily (18, 36, or 54 mg) and placebo. Studies 1 and 2 involved a 3-way crossover of 1 week per treatment arm. Study 3 involved 4 weeks of parallel-group treatments with a Last Observation Carried Forward analysis at week 4. Error bars represent the mean plus standard error of the mean.

In Studies 1 and 2, symptoms of ADHD were evaluated by laboratory schoolteachers using the SKAMP [Swanson, Kotkin, Agler, M-Fynn, and Pelham] laboratory school rating scale. The combined results from these two studies demonstrated statistically significant improvements in attention and behavior in patients treated with CONCERTA® versus placebo that were maintained through 12 hours after dosing. Figure 3 presents the laboratory schoolteacher SKAMP ratings for CONCERTA® and placebo.

Figure 3: Laboratory School Teacher SKAMP Ratings: Mean (SEM) of Combined Attention (Studies 1 and 2)

14.2 Adolescents

In a randomized, double-blind, multicenter, placebo-controlled trial (Study 4) involving 177 patients, CONCERTA® was demonstrated to be effective in the treatment of ADHD in adolescents aged 13 to 18 years at doses up to 72 mg/day (1.4 mg/kg/day). Of 220 patients who entered an open 4-week titration phase, 177 were titrated to an individualized dose (maximum of 72 mg/day) based on meeting specific improvement criteria on the ADHD Rating Scale and the Global Assessment of Effectiveness with acceptable tolerability. Patients who met these criteria were then randomized to receive either their individualized dose of CONCERTA® (18 – 72 mg/day, n=87) or placebo (n=90) during a two-week double-blind phase. At the end of this phase, mean scores for the investigator rating on the ADHD Rating Scale demonstrated that CONCERTA® was statistically significantly superior to placebo.

14.3 Adults

Two double-blind, placebo-controlled studies were conducted in 627 adults aged 18 to 65 years. The controlled studies compared CONCERTA® administered once daily and placebo in a multicenter, parallel-group, 7-week dose-titration study (Study 5) (36 to 108 mg/day) and in a multicenter, parallel-group, 5-week, fixed-dose study (Study 6) (18, 36, and 72 mg/day).

Study 5 demonstrated the effectiveness of CONCERTA® in the treatment of ADHD in adults aged 18 to 65 years at doses from 36 mg/day to 108 mg/day based on the change from baseline to final study visit on the Adult ADHD Investigator Rating Scale (AISRS). Of 226 patients who entered the 7-week trial, 110 were randomized to CONCERTA® and 116 were randomized to placebo. Treatment was initiated at 36 mg/day and patients continued with incremental increases of 18 mg/day (36 to 108 mg/day) based on meeting specific improvement criteria with acceptable tolerability. At the final study visit, mean change scores (LS Mean, SEM) for the investigator rating on the AISRS demonstrated that CONCERTA® was statistically significantly superior to placebo.

Study 6 was a multicenter, double-blind, randomized, placebo-controlled, parallel-group, dose-response study (5-week duration) with 3 fixed-dose groups (18, 36, and 72 mg). Patients were randomized to receive CONCERTA® administered at doses of 18 mg (n=101), 36 mg (n=102), 72 mg/day (n=102), or placebo (n=96). All three doses of CONCERTA® were statistically significantly more effective than placebo in improving CAARS (Conners' Adult ADHD Rating Scale) total scores at double-blind end point in adult subjects with ADHD.

15 REFERENCES

American Psychiatric Association. Diagnostic and Statistical Manual of Mental Disorders. 4th ed. Washington, DC: American Psychiatric Association, 1994.

16 HOW SUPPLIED/STORAGE AND HANDLING

CONCERTA® (methylphenidate HCl) Extended-release Tablets are available in 18-mg, 27-mg, 36-mg, and 54-mg dosage strengths. The 18-mg tablets are yellow and imprinted with "alza 18." The 27-mg tablets are gray and imprinted with "alza 27." The 36-mg tablets are white and imprinted with "alza 36." The 54-mg tablets are brownish-red and imprinted with "alza 54." All four dosage strengths are supplied in

18 mg
Bottles of 10 | NDC 54868-4489-0
Bottles of 30 | NDC 54868-4489-2
Bottles of 60 | NDC 54868-4489-3
Bottles of 90 | NDC 54868-4489-1

27 mg
Bottles of 10 | NDC 54868-4957-0
Bottles of 30 | NDC 54868-4957-1

36 mg
Bottles of 10 | NDC 54868-4759-3
Bottles of 20 | NDC 54868-4759-1
Bottles of 30 | NDC 54868-4759-2
Bottles of 60 | NDC 54868-4759-0

54 mg
Bottles of 10 | NDC 54868-4789-1
Bottles of 30 | NDC 54868-4789-0

Storage and Handling

Store at 25°C (77°F); excursions permitted to 15–30°C (59–86°F) [see USP Controlled Room Temperature]. Protect from humidity.

17 PATIENT COUNSELING INFORMATION

See Medication Guide

17.1 Information for Patients

Prescribers or other health professionals should inform patients, their families, and their caregivers about the benefits and risks associated with treatment with methylphenidate and should counsel them in its appropriate use. A patient Medication Guide is available for CONCERTA®. The prescriber or health professional should instruct patients, their families, and their caregivers to read the Medication Guide and should assist them in understanding its contents. Patients should be given the opportunity to discuss the contents of the Medication Guide and to obtain answers to any questions they may have. The complete text of the Medication Guide is reprinted at the end of this document.

Patients should be informed that CONCERTA® should be swallowed whole with the aid of liquids. Tablets should not be chewed, divided, or crushed. The medication is contained within a nonabsorbable shell designed to release the drug at a controlled rate. The tablet shell, along with insoluble core components, is eliminated from the body; patients should not be concerned if they occasionally notice in their stool something that looks like a tablet.

Stimulants may impair the ability of the patient to operate potentially hazardous machinery or vehicles. Patients should be cautioned accordingly until they are reasonably certain that CONCERTA® does not adversely affect their ability to engage in such activities.

For more information call 1-888-440-7903.

Manufactured for:
McNeil Pediatrics, Division of Ortho-McNeil-Janssen Pharmaceuticals, Inc.
Titusville, NJ 08560

10180604

Revised: November 2010

Relabeling and Repackaging by:
Physicians Total Care, Inc.
Tulsa, OK 74146

MEDICATION GUIDE
CONCERTA® (kon SER-ta)
(methylphenidate HCl) Extended-release Tablets CII

Read the Medication Guide that comes with CONCERTA® before you or your child starts taking it and each time you get a refill. There may be new information. This Medication Guide does not take the place of talking to your doctor about your or your child's treatment with CONCERTA®.

BOXED WARNING

What is the most important information I should know about CONCERTA®?

The following have been reported with use of methylphenidate HCl and other stimulant medicines:

1. Heart-related problems:

- sudden death in patients who have heart problems or heart defects
- stroke and heart attack in adults
- increased blood pressure and heart rate

Tell your doctor if you or your child has any heart problems, heart defects, high blood pressure, or a family history of these problems.

Your doctor should check you or your child carefully for heart problems before starting CONCERTA®.

Your doctor should check you or your child's blood pressure and heart rate regularly during treatment with CONCERTA®.

Call your doctor right away if you or your child has any signs of heart problems such as chest pain, shortness of breath, or fainting while taking CONCERTA®.

2. Mental (Psychiatric) problems:

All Patients

- new or worse behavior and thought problems
- new or worse bipolar illness
- new or worse aggressive behavior or hostility

Children and Teenagers

- new psychotic symptoms (such as hearing voices, believing things that are not true, are suspicious) or new manic symptoms

Tell your doctor about any mental problems you or your child have, or about a family history of suicide, bipolar illness, or depression.

Call your doctor right away if you or your child has any new or worsening mental symptoms or problems while taking CONCERTA®, especially seeing or hearing things that are not real, believing things that are not real, or are suspicious.

What Is CONCERTA®?

CONCERTA® is a central nervous system stimulant prescription medicine. It is used for the treatment of attention deficit and hyperactivity disorder (ADHD). CONCERTA® may help increase attention and decrease impulsiveness and hyperactivity in patients with ADHD.

CONCERTA® should be used as a part of a total treatment program for ADHD that may include counseling or other therapies.

BOXED WARNING

CONCERTA® is a federally controlled substance (CII) because it can be abused or lead to dependence. Keep CONCERTA® in a safe place to prevent misuse and abuse. Selling or giving away CONCERTA® may harm others, and is against the law.

Tell your doctor if you or your child have (or have a family history of) ever abused or been dependent on alcohol, prescription medicines, or street drugs.

Who should not take CONCERTA®?

CONCERTA® should not be taken if you or your child:

- are very anxious, tense, or agitated
- have an eye problem called glaucoma
- have tics or Tourette's syndrome, or a family history of Tourette's syndrome. Tics are hard-to-control repeated movements or sounds.
- are taking or have taken within the past 14 days an antidepression medicine called a monoamine oxidase inhibitor or MAOI.
- are allergic to anything in CONCERTA®. See the end of this Medication Guide for a complete list of ingredients.

CONCERTA® should not be used in children less than 6 years old because it has not been studied in this age group.

CONCERTA® may not be right for you or your child. Before starting CONCERTA®, tell your or your child's doctor about all health conditions (or a family history of) including:

- heart problems, heart defects, or high blood pressure
- mental problems including psychosis, mania, bipolar illness, or depression
- tics or Tourette's syndrome
- seizures or have had an abnormal brain wave test (EEG)
- esophagus, stomach, or small or large intestine problems

Tell your doctor if you or your child is pregnant, planning to become pregnant, or breastfeeding.

Can CONCERTA® be taken with other medicines?

Tell your doctor about all of the medicines that you or your child take including prescription and nonprescription medicines, vitamins, and herbal supplements. CONCERTA® and some medicines may interact with each other and cause serious side effects. Sometimes the doses of other medicines will need to be adjusted while taking CONCERTA®.

Your doctor will decide whether CONCERTA® can be taken with other medicines.

Especially tell your doctor if you or your child takes:

- antidepression medicines including MAOIs
- seizure medicines
- blood thinner medicines
- blood pressure medicines
- cold or allergy medicines that contain decongestants

Know the medicines that you or your child takes. Keep a list of your medicines with you to show your doctor and pharmacist.

Do not start any new medicine while taking CONCERTA® without talking to your doctor first.

How should CONCERTA® be taken?

- Take CONCERTA® exactly as prescribed. Your doctor may adjust the dose until it is right for you or your child.
- Do not chew, crush, or divide the tablets. Swallow CONCERTA® tablets whole with water or other liquids. Tell your doctor if you or your child cannot swallow CONCERTA® whole. A different medicine may need to be prescribed.
- CONCERTA® can be taken with or without food.
- Take CONCERTA® once each day in the morning. CONCERTA® is an extended-release tablet. It releases medication into your/your child's body throughout the day.
- The CONCERTA® tablet does not dissolve completely in the body after all the medicine has been released. You or your child may sometimes notice the empty tablet in a bowel movement. This is normal.
- From time to time, your doctor may stop CONCERTA® treatment for a while to check ADHD symptoms.
- Your doctor may do regular checks of the blood, heart, and blood pressure while taking CONCERTA®. Children should have their height and weight checked often while taking CONCERTA®. CONCERTA® treatment may be stopped if a problem is found during these check-ups.
- If you or your child takes too much CONCERTA® or overdoses, call your doctor or poison control center right away, or get emergency treatment.

What are possible side effects of CONCERTA®?

See "What is the most important information I should know about CONCERTA®?" for information on reported heart and mental problems.

Other serious side effects include:

- slowing of growth (height and weight) in children
- seizures, mainly in patients with a history of seizures
- eyesight changes or blurred vision
- blockage of the esophagus, stomach, small or large intestine in patients who already have a narrowing in any of these organs

Common side effects include:

- decreased appetite
- dry mouth
- trouble sleeping
- dizziness
- stomach ache
- increased sweating

- headache
- nausea
- anxiety
- weight loss
- irritability

Stimulants may impair the ability of you or your child to operate potentially hazardous machinery or vehicles. You or your child should exercise caution until you/your child is reasonably certain that CONCERTA® does not adversely affect your/your child's ability to engage in such activities.

Talk to your doctor if you or your child has side effects that are bothersome or do not go away.

This is not a complete list of possible side effects. Ask your doctor or pharmacist for more information.

Call your doctor for medical advice about side effects. You may report side effects to FDA at 1-800-FDA-1088.

You may also report side effects to McNeil Pediatrics at 1-888-440-7903.

How should I store CONCERTA®?

- Store CONCERTA® in a safe place at room temperature, 59 to 86° F (15 to 30° C). Protect from moisture.
- Keep CONCERTA® and all medicines out of the reach of children.

General information about CONCERTA®

Medicines are sometimes prescribed for purposes other than those listed in a Medication Guide. Do not use CONCERTA® for a condition for which it was not prescribed. Do not give CONCERTA® to other people, even if they have the same condition. It may harm them and it is against the law.

This Medication Guide summarizes the most important information about CONCERTA®. If you would like more information, talk with your doctor. You can ask your doctor or pharmacist for information about CONCERTA® that was written for healthcare professionals. For more information about CONCERTA® call 1-888-440-7903.

What are the ingredients in CONCERTA®?

Active Ingredient: methylphenidate HCl

Inactive Ingredients: butylated hydroxytoluene, carnauba wax, cellulose acetate, hypromellose, lactose, phosphoric acid, poloxamer, polyethylene glycol, polyethylene oxides, povidone, propylene glycol, sodium chloride, stearic acid, succinic acid, synthetic iron oxides, titanium dioxide, and triacetin.

This Medication Guide has been approved by the U.S. Food and Drug Administration.

Manufactured for:
McNeil Pediatrics
Division of Ortho-McNeil-Janssen Pharmaceuticals, Inc., Titusville, NJ 08560

10180602
Revised: November 2010

PRINCIPAL DISPLAY PANEL - 18 mg Tablet Label

CONCERTA®
(methylphenidate HCl)
CII

Extended-release tablets

18 mg

Each tablet contains 18 mg
methylphenidate hydrochloride
in a controlled-release formulation.

Rx only

Please see the Medication Guide
provided by your pharmacist.

PRINCIPAL DISPLAY PANEL - 27 mg Tablet Label

CONCERTA®
(methylphenidate HCl)
CII

Extended-release tablets

27 mg

Each tablet contains 27 mg
methylphenidate hydrochloride
in a controlled-release formulation.

Rx only

Please see the Medication Guide
provided by your pharmacist.

PRINCIPAL DISPLAY PANEL - 36 mg Tablet Label

CONCERTA®
(methylphenidate HCl)
CII

Extended-release tablets

36 mg

Each tablet contains 36 mg
methylphenidate hydrochloride
in a controlled-release formulation.

Rx only

Please see the Medication Guide
provided by your pharmacist.

PRINCIPAL DISPLAY PANEL - 54 mg Tablet Label

CONCERTA®
(methylphenidate HCl)
CII

Extended-release tablets

54 mg

Each tablet contains 54 mg
methylphenidate hydrochloride
in a controlled-release formulation.

Rx only

Please see the Medication Guide
provided by your pharmacist.